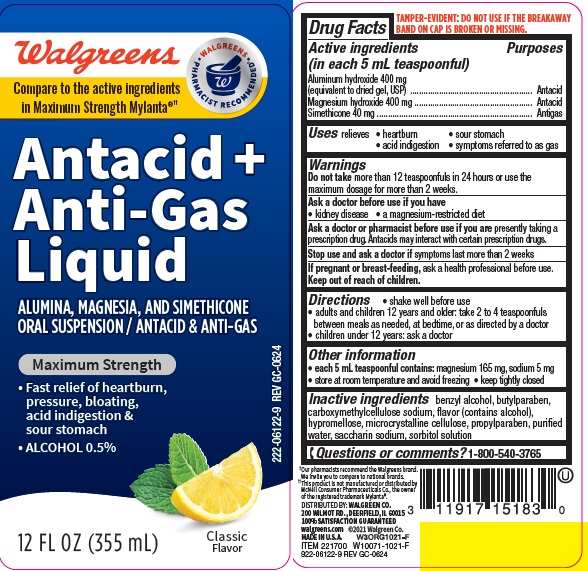 DRUG LABEL: MAXIMUM STRENGTH ANTACID ANTIGAS
NDC: 0363-1691 | Form: SUSPENSION
Manufacturer: WALGREEN COMPANY
Category: otc | Type: HUMAN OTC DRUG LABEL
Date: 20251119

ACTIVE INGREDIENTS: ALUMINUM HYDROXIDE 400 mg/5 mL; MAGNESIUM HYDROXIDE 400 mg/5 mL; DIMETHICONE 40 mg/5 mL
INACTIVE INGREDIENTS: BUTYLPARABEN; CARBOXYMETHYLCELLULOSE SODIUM; BENZYL ALCOHOL; HYPROMELLOSES; CELLULOSE, MICROCRYSTALLINE; PROPYLPARABEN; WATER; SACCHARIN SODIUM; SORBITOL

WALgreens max antacid

Active ingredients (in each 5 mL teaspoonful)

Aluminum hydroxide 400 mg (equivalent to dried gel, USP)

Magnesium hydroxide 400 mg

Simethicone 40mg

Purposes

Antacid

Antigas

Uses

relieves

- heartburn
- sour stomach
- acid indigestion
- the symptoms referred to as gas

Warnings

Do not take more than 12 teaspoonfuls in 24 hours or use the
maximum dosage for more than 2 weeks.

Ask a doctor before use if you have

- kidney disease
- a magnesium-restricted diet

Ask a doctor or pharmacist before use if you are taking a prescription drug.

Antacids may interact with certain prescription drugs.

Stop use and ask a doctor if symptoms last more than 2 weeks

If pregnant or breast-feeding, ask a health professional before use.

Keep out of reach of children.

Directions

- shake well before use
- adults and children 12 years and older: take 2 to 4 teaspoonfuls between meals, at bedtime, or as directed by a doctor
- children under 12 years of age: ask a doctor

Other information

- each 5 mL teaspoonful contains: magnesium 165 mg, sodium 5 mg
- store at room temperature and avoid freezing
- keep tightly closed

Inactive ingredients

benzyl alcohol, butylparaben, carboxymethylcellulose sodium, flavor (contains alcohol), hypromellose, microcrystalline cellulose, propylparaben, purified water, saccharin sodium, sorbitol solution

Questions or comments?

1-800-540-3765